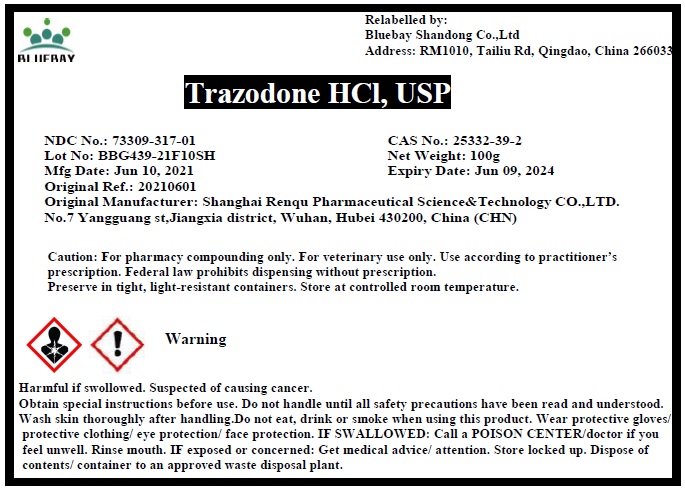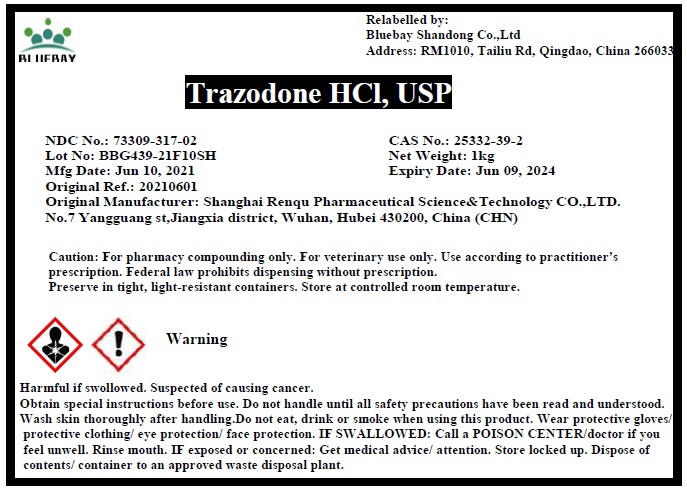 DRUG LABEL: Trazodone HCl
NDC: 73309-317 | Form: POWDER
Manufacturer: BLUEBAY SHANDONG CO.,LTD
Category: other | Type: BULK INGREDIENT
Date: 20210922

ACTIVE INGREDIENTS: TRAZODONE HYDROCHLORIDE 1 g/1 g

Trazodone HCl